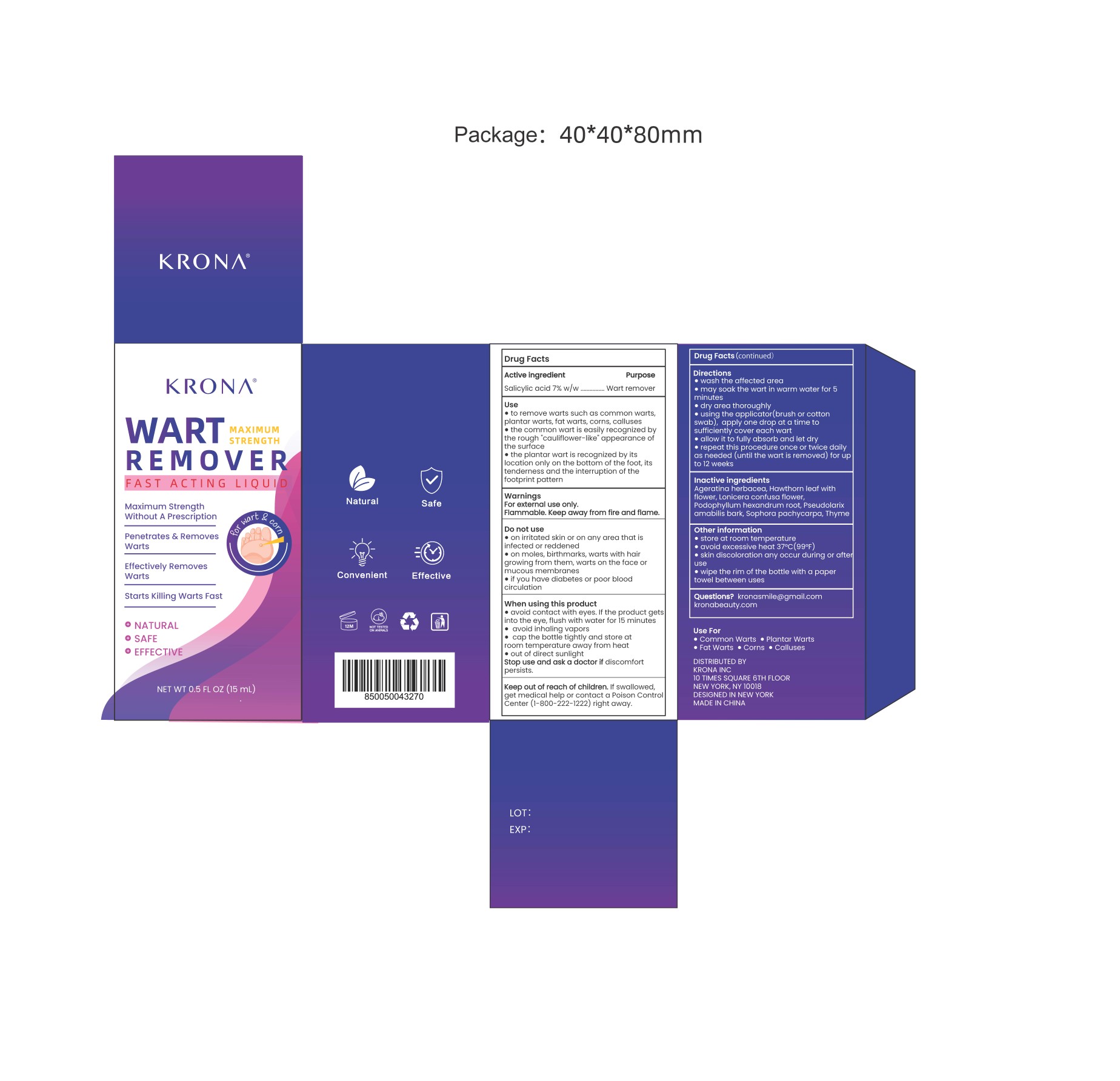 DRUG LABEL: WART REMOVER
NDC: 83299-006 | Form: LIQUID
Manufacturer: Consilii LLC
Category: otc | Type: HUMAN OTC DRUG LABEL
Date: 20230603

ACTIVE INGREDIENTS: METHYL SALICYLATE 7 g/100 mL
INACTIVE INGREDIENTS: HAWTHORN LEAF WITH FLOWER; SOPHORA FLAVESCENS ROOT; PSEUDOLARIX AMABILIS BARK; STELLERA CHAMAEJASME WHOLE; LONICERA CONFUSA FLOWER; CNIDIUM MONNIERI FRUIT; PODOPHYLLUM

Active Ingredient

Salicylic acid 7%

Purpose

Wart remover

Use

to remove warts such as common warts, plantar warts, fat warts, corns, calluses
the common wart is easily recognized by the rough "cauliflower-like" appearance of the surface
the plantar wart is recognized by its location only on the bottom of the foot, its tenderness and the interruption of the footprint pattern

Warnings

For external use only.
Flammable. Keep away from fire and flame.

Do not use

on irritated skin or on any area that is infected or reddened
on moles, birthmarks, warts with hair growing from them, warts on the face or mucous membranes
if you have diabetes or poor blood circulation

When Using

avoid contact with eyes. If the product gets into the eye, flush with water for 15 minutes
avoid inhaling vapors
cap the bottle tightly and store at room temperature away from heat
out of direct sunlight

Stop Use

if discomfort persists.

Ask Doctor

if discomfort persists.

Keep Oot Of Reach Of Children

If swallowed, get medical help or contact a Poison Control Center (1-800-222-1222) right away.

Directions

wash the affected area
may soak the wart in warm water for 5 minutes
dry area thoroughly
using the applicator(brush or cotton swab), apply one drop at a time to sufficiently cover each wart
allow it to fully absorb and let dry
repeat this procedure once or twice daily as needed (until the wart is removed) for up to 12 weeks

Other information

store at room temperature
avoid excessive heat 37°C(99°F)
skin discoloration any occur during or after use
wipe the rim of the bottle with a paper towel between uses

Inactive ingredients

Ageratina herbacea, Hawthorn leaf with flower, Lonicera confusa flower, Podophyllum hexandrum root, Pseudolarix amabilis bark, Sophora pachycarpa, Thyme

Questions

kronasmile@gmail.com

kronabeauty.com